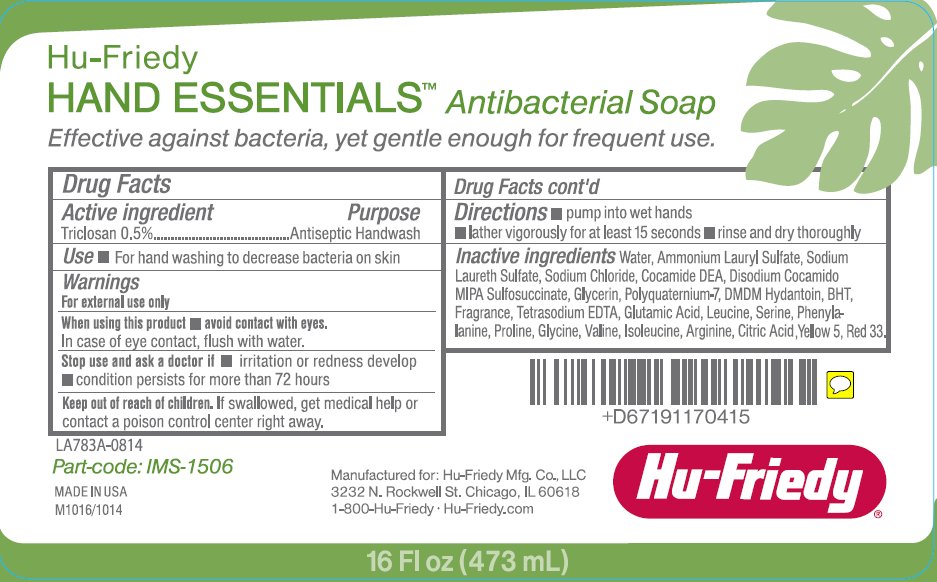 DRUG LABEL: Hand Essentials Antibacterial
NDC: 65626-017 | Form: SOAP
Manufacturer: HU-FRIEDY MFG. CO., INC.
Category: otc | Type: HUMAN OTC DRUG LABEL
Date: 20150219

ACTIVE INGREDIENTS: TRICLOSAN 0.5 mg/100 mL
INACTIVE INGREDIENTS: WATER; AMMONIUM LAURYL SULFATE; SODIUM LAURETH-3 SULFATE; SODIUM CHLORIDE; COCO DIETHANOLAMIDE; POLYQUATERNIUM-7 (76/24 ACRYLAMIDE/DADMAC; 120000 MW); GLYCERIN; DMDM HYDANTOIN; BUTYLATED HYDROXYTOLUENE; EDETATE SODIUM; GLUTAMIC ACID; LEUCINE; SERINE; PHENYLALANINE; PROLINE; GLYCINE; VALINE; ISOLEUCINE; ARGININE; CITRIC ACID MONOHYDRATE; FD&C YELLOW NO. 5; D&C RED NO. 33

Drug Facts

Active ingredient

Triclosan 0.5%

Purpose

Antiseptic Handwash

Uses

- For handwashing to decrease bacteria on skin

Warnings

For external use only.

When using this product

- avoid contact with eyes. In case of eye contact, flush with water.

Stop use and ask a doctor if

- irritation or redness develop
- condition persists for more than 72 hours

Keep out of reach of children.

- If swallowed, get medical help or contact a poison control center right away.

Directions

- pump into wet hands
- lather vigorously for at least 15 seconds
- rinse and dry thoroughly

Inactive ingredients

Water, Ammonium Lauryl Sulfate, Sodium Laureth Sulfate, Sodium Chloride, Cocamide DEA, Disodium Cocamido MIPA Sulfosuccinate, Glycerin, Polyquaternium-7, DMDM Hydantoin, BHT, Fragrance, Tetrasodium EDTA, Glutamic Acid, Leucine, Serine, Phenylalanine, Proline, Glycine, Valine, Isoleucine, Arginine, Citric Acid., Yellow 5, Red 33

Package/Label Principal Display Panel

Hu-Friedy

HAND ESSENTIALS

Antibacterial Soap

Effective against bacteria, yet gentle enough for frequent use.

Part-code: IMS-1506

MADE IN USA

Hu-Friedy

16 Fl oz (473 mL)